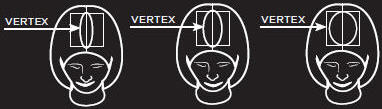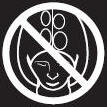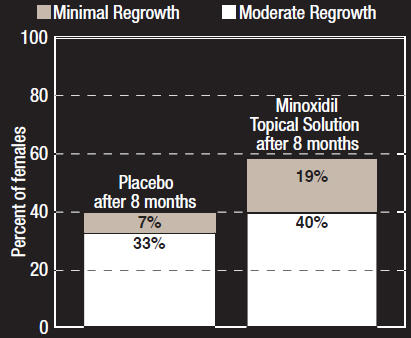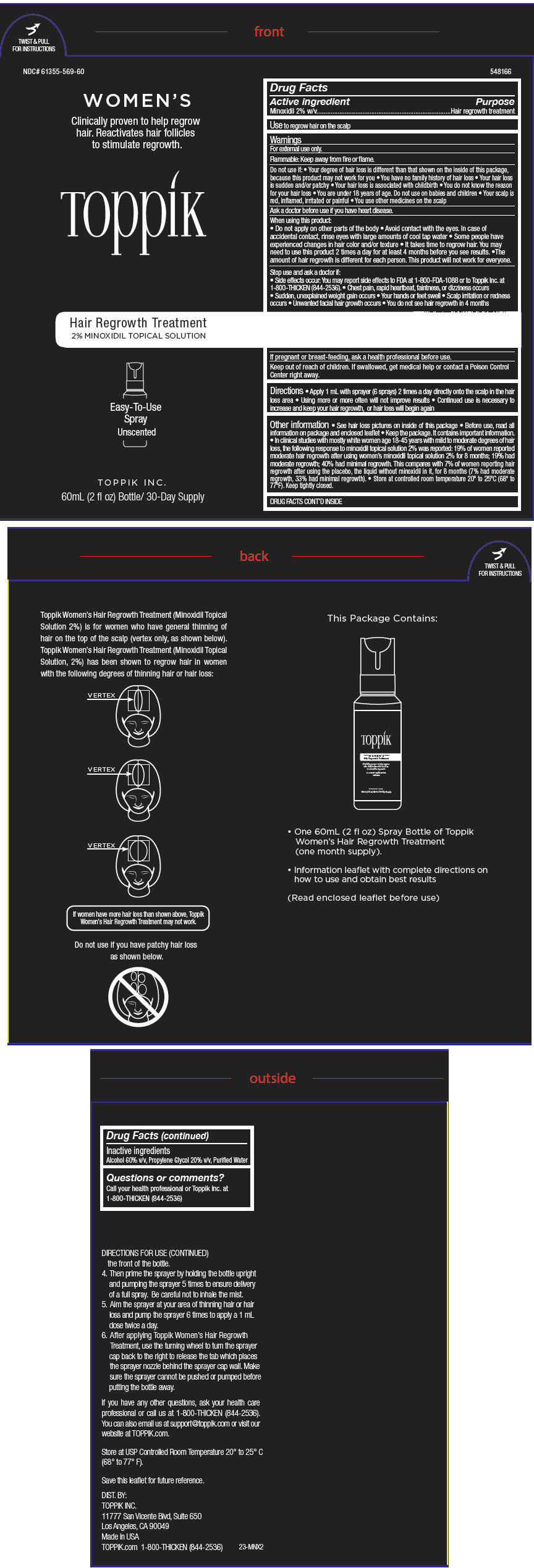 DRUG LABEL: Toppik Womens Hair Regrowth Treatment
NDC: 61355-569 | Form: SOLUTION
Manufacturer: Spencer Forrest, Inc.
Category: otc | Type: HUMAN OTC DRUG LABEL
Date: 20140507

ACTIVE INGREDIENTS: Minoxidil 20 mg/1 mL
INACTIVE INGREDIENTS: Alcohol; Propylene Glycol; Water

Toppik Women's Hair Regrowth Treatment

Drug Facts

Active ingredient

Minoxidil 2% w/v

Purpose

Hair regrowth treatment

Use

to regrow hair on the scalp

Warnings

For external use only.

Flammable: Keep away from fire or flame.

Do not use if:

- Your degree of hair loss is different than that shown on the inside of this package, because this product may not work for you
- You have no family history of hair loss
- Your hair loss is sudden and/or patchy
- Your hair loss is associated with childbirth
- You do not know the reason for your hair loss
- You are under 18 years of age. Do not use on babies and children
- Your scalp is red, inflamed, irritated or painful
- You use other medicines on the scalp

Ask a doctor before use if you have heart disease.

When using this product:

- Do not apply on other parts of the body
- Avoid contact with the eyes. In case of accidental contact, rinse eyes with large amounts of cool tap water
- Some people have experienced changes in hair color and/or texture
- It takes time to regrow hair. You may need to use this product 2 times a day for at least 4 months before you see results.
- The amount of hair regrowth is different for each person. This product will not work for everyone.

Stop use and ask a doctor if:

- Side effects occur: You may report side effects to FDA at 1-800-FDA-1088 or to Toppik Inc. at 1-800-THICKEN (844-2536).
- Chest pain, rapid heartbeat, faintness, or dizziness occurs
- Sudden, unexplained weight gain occurs
- Your hands or feet swell
- Scalp irritation or redness occurs
- Unwanted facial hair growth occurs
- You do not see hair regrowth in 4 months

PREGNANCY OR BREAST FEEDING

If pregnant or breast-feeding, ask a health professional before use.

Keep out of reach of children. If swallowed, get medical help or contact a Poison Control Center right away.

Directions

- Apply 1 mL with sprayer (6 sprays) 2 times a day directly onto the scalp in the hair loss area
- Using more or more often will not improve results
- Continued use is necessary to increase and keep your hair regrowth, or hair loss will begin again

Other information

- See hair loss pictures on inside of this package
- Before use, read all information on package and enclosed leaflet
- Keep the package. It contains important information.
- In clinical studies with mostly white women age 18-45 years with mild to moderate degrees of hair loss, the following response to minoxidil topical solution 2% was reported: 19% of women reported moderate hair regrowth after using women's minoxidil topical solution 2% for 8 months; 19% had moderate regrowth; 40% had minimal regrowth. This compares with 7% of women reporting hair regrowth after using the placebo, the liquid without minoxidil in it, for 8 months (7% had moderate regrowth, 33% had minimal regrowth).
- Store at controlled room temperature 20° to 25°C (68° to 77°F). Keep tightly closed.

Inactive ingredients

Alcohol 60% v/v, Propylene Glycol 20% v/v, Purified Water

Questions or comments?

Call your health professional or Toppik Inc. at 1-800-THICKEN (844-2536)

DIST. BY:
TOPPIK INC.
11777 San Vicente Blvd, Suite 650
Los Angeles, CA 90049

PATIENT INFORMATION

Toppik
Hair Regrowth Treatment
WOMEN'S
2% Minoxidil Topical Solution
Unscented

Important information about Toppik Women's Hair Regrowth Treatment Minoxidil Topical Solution USP 2%

Save this leaflet for future reference.

- Hair regrowth treatment
- Previously available only by prescription

Over 30 million American women experience hair thinning or hair loss, so you're not alone. Toppik Women's Hair Regrowth Treatment contains the only ingredient that is medically proven effective to help regrow hair in women.

Please read this leaflet carefully. It will help you understand how to use Toppik Women's Hair Regrowth Treatment and what to expect from its use. If you have any questions after reading this leaflet, or anytime while using Toppik Women's Hair Regrowth Treatment, you should ask your health care professional or call us at 1-800-THICKEN (844-2536). You can also contact us via email at support@toppik.com or on our website at TOPPIK.com.

What is Toppik Women's Hair Regrowth Treatment?

Toppik Women's Hair Regrowth Treatment is a colorless liquid medication for use only on the scalp to help regrow hair.

Who may use Toppik Women's Hair Regrowth Treatment ?

Toppik Women's Hair Regrowth Treatment may be appropriate for you if you are an adult at least 18 years old and experiencing gradually thinning hair or gradual hair loss on the top of the head. The common hereditary thinning or hair loss process begins slowly and may become noticeable only after years of gradual loss. Toppik Women's Hair Regrowth Treatment is for general thinning of hair on the top of the scalp as shown in the illustration. Toppik Women's Hair Regrowth Treatment

has been shown to regrow hair in women with the degrees of hair loss shown. If women have more hair loss than shown, Toppik Women's Hair Regrowth Treatment may not work. Many of those experiencing hair loss have other family members with gradual thinning hair or hair loss. If there is no family history of gradual thinning hair or gradual hair loss, or your hair loss is patchy, see your doctor.

Who should NOT use Toppik Women's Hair Regrowth Treatment?

Toppik Women's Hair Regrowth Treatment will not prevent or improve hair loss related to pregnancy, the use of some prescription and non-prescription medications, certain severe nutritional problems (very low body iron; excessive vitamin A intake), the recently discontinued use of birth control pills, low thyroid states (hypothyroidism), chemotherapy, or diseases which cause scarring of the scalp.

Also, Toppik Women's Hair Regrowth Treatment will not improve hair loss due to:

- Damage from the use of hair care products which cause scarring or deep burns of the scalp.
- Hair grooming methods such as cornrowing or ponytails which require pulling the hair tightly back from the scalp.

Do not use Toppik Women's Hair Regrowth Treatment if hair loss is patchy as shown below.

You should ask your doctor if you are unsure of the cause of your hair loss

Will Toppik Women's Hair Regrowth Treatment work for me?

The amount of hair regrowth is different for each person. Not everyone will respond to Toppik Women's Hair Regrowth Treatment. The response to Toppik Women's Hair Regrowth Treatment cannot be predicted. No one will be able to grow back all their hair. In clinical studies of mostly white women aged 18-45 years with mild to moderate degrees of hair loss, the following response to Minoxidil Topical Solution 2% was reported:

Female Response to Minoxidil Topical Solution 2% Percent reporting hair regrowth

19% of women reported moderate hair regrowth after using Minoxidil Topical Solution 2% for 8 months (19% had moderate regrowth; 40% had minimal regrowth). This compares with 7% of women reporting moderate hair regrowth after using placebo, the liquid without minoxidil in it, for 8 months (7% had moderate regrowth; 33% had minimal regrowth).

What Minimal, Moderate and Dense Hair Regrowth Will Mean For You?

 | Number of Hairs | Hair Density
Minimal | Some new hairs are seen, but not enough to cover thinning areas. | Hairs in thinning areas do not grow as closely together as hairs on the rest of the head.
Moderate | New hairs cover some or all of the thinning areas. | Hairs in the thinning areas grow more closely together but are not as close together as hairs on the rest of the head.
Dense | New hairs cover, or almost completely cover, thinning areas. | Hairs in the thinning areas grow as closely together as hair on the rest of the head.

Can Toppik Women's Hair Regrowth Treatment be used to prevent hair loss?

We do not know if Toppik Women's Hair Regrowth Treatment will prevent hair loss.

How soon can I expect results from using Toppik Women's Hair Regrowth Treatment?

Since normal hair usually grows only 1/2 to 1 inch per month, hair regrowth with Toppik Women's Hair Regrowth Treatment also takes time. Generally new hair growth is slow for a Toppik Women's Hair Regrowth Treatment user. Continued use of 2 times a day for at least 4 months is usually needed before you notice hair regrowth. If you do not see hair regrowth in 4 months, stop using Toppik Women's Hair Regrowth Treatment and see your doctor.

When you first begin to use Toppik Women's Hair Regrowth Treatment, your hair loss may continue for up to 2 weeks. This hair loss is temporary. If you continue to lose hair after two weeks, see your doctor.

If Toppik Women's Hair Regrowth Treatment is working, what will the hair look like?

At first, hair growth is usually soft, downy, colorless hairs (like peach fuzz). After further use, the new hairs should be the same color and thickness as the other hairs on your scalp.

How long do I need to use Toppik Women's Hair Regrowth Treatment?

If you respond to Toppik Women's Hair Regrowth Treatment, you need to use it 2 times a day to keep and continue the hair regrowth. Up to 8 months of usage may be needed to see your best results from Toppik Women's Hair Regrowth Treatment.

What happens if I completely stop using Toppik Women's Hair Regrowth Treatment? Will I keep the new hair?

Continuous use of Toppik Women's Hair Regrowth Treatment is needed to maintain hair regrowth. If you stop using Toppik Women's Hair Regrowth Treatment, the normal hair loss process will start again. You will probably lose your newly regrown hair in three to four months.

What is the dosage of Toppik Women's Hair Regrowth Treatment?

You should apply a dose (1mL) of Toppik Women's Hair Regrowth Treatment directly onto scalp in the hair loss area TWO TIMES A DAY; for example, once in the morning and once at the night. Each bottle should last about one month, if used as directed. Please refer to the "Directions for Use" section of the leaflet.

What if I miss a dose or forget to use Toppik Women's Hair Regrowth Treatment?

If you miss one or two daily doses of Toppik Women's Hair Regrowth Treatment, just continue with your next dose. You should not make up for missed doses.

Can I use Toppik Women's Hair Regrowth Treatment more than twice a day? Will it work faster, better?

No. Toppik Women's Hair Regrowth Treatment will not work faster or better if used more than two times a day. Studies have been carefully conducted to determine the correct amount of Toppik Women's Hair Regrowth Treatment needed to get the best results. More frequent use or larger doses have not been shown to speed up hair growth and may increase your chance of side effects.

What are most common side effects with Toppik Women's Hair Regrowth Treatment?

The most common side effects are itching and other skin irritations of the treated area of the scalp. Toppik Women's Hair Regrowth Treatment contains alcohol, which would cause burning or irritation of the eyes or sensitive skin areas. If Toppik Women's Hair Regrowth Treatment accidentally gets into these areas, rinse with large amounts of cool tap water. Consult your doctor if irritation persists.

What kind of shampoo should I use with Toppik Women's Hair Regrowth Treatment?

If you wash your scalp before applying Toppik Women's Hair Regrowth Treatment, use a mild shampoo.

Can I use hair sprays, mousses, conditioners, gels, etc.?

Yes. There is no reason to change your usual hair care routine when using Toppik Women's Hair Regrowth Treatment. However, you should apply Toppik Women's Hair Regrowth Treatment first and wait for it to dry before using your styling aids.

Can I have my hair colored or permed or use hair relaxers while using Toppik Women's Hair Regrowth Treatment?

Yes. We have no information that these treatments change the effect of Toppik Women's Hair Regrowth Treatment. However, to avoid possible scalp irritation, you should make sure all of the Toppik Women's Hair Regrowth Treatment has been washed off the hair and scalp before using color or perm chemicals.

Can I apply Toppik Women's Hair Regrowth Treatment and wash my hair an hour later?

No. For Toppik Women's Hair Regrowth Treatment to work best, you should allow it to remain on the scalp for about 4 hours before washing.

Can I go swimming or out in the rain?

Yes. Avoid washing off the Toppik Women's Hair Regrowth Treatment. If possible, apply Toppik Women's Hair Regrowth Treatment to a dry scalp after swimming, or wait about 4 hours after application before going swimming. Do not let your scalp get wet from the rain after applying Toppik Women's Hair Regrowth Treatment.

Can Toppik Women's Hair Regrowth Treatment produce unwanted hair?

Although unwanted hair growth has been reported on the face and on other parts of the body, such reports have been infrequent. The unwanted hair growth may be caused by the transfer of Toppik Women's Hair Regrowth Treatment to areas other than the scalp, or by absorption into the circulatory system of low levels of the active ingredient, or by a medical condition not related to the use of Toppik Women's Hair Regrowth Treatment. If you experience unwanted hair, discontinue using Toppik Women's Hair Regrowth Treatment and see your doctor for recommendations about appropriate treatment. After stopping use of Toppik Women's Hair Regrowth Treatment, the unwanted hair, if caused by the use of Toppik Women's Hair Regrowth Treatment, should go away over time.

You can take steps to decrease the chances for unwanted hair growth:

1. Limit the application of Toppik Women's Hair Regrowth Treatment only to the scalp,
2. If you use your hands to apply Toppik Women's Hair Regrowth Treatment, wash your hands thoroughly afterwards, and
3. Allow sufficient drying time (usually 2 to 4 hours before going to bed) after your nighttime application of Toppik Women's Hair Regrowth Treatment.

Can I use Toppik Women's Hair Regrowth Treatment for baldness or hair loss in babies and children?

No. Toppik Women's Hair Regrowth Treatment must not be used to treat baldness or hair loss in babies or children.

Are there special warnings about the use of Toppik Women's Hair Regrowth Treatment?

For external use only.

Flammable: Keep away from fire or flame.

Do not use if:

- Your degree of hair loss is more than that shown in the illustration on page 1 of this leaflet, because this product may not work for you.
- You have no family history of hair loss.
- Your hair loss is sudden and/or patchy.
- Your hair loss is associated with childbirth.
- You do not know the reason for your hair loss.
- You are under 18 years of age. Do not use on babies and children.
- Your scalp is red, inflamed, infected, irritated, or painful.
- You use other medicines on the scalp.

Ask a doctor before use if you have heart disease.

When using this product:

- Do not apply on other parts of the body.
- Avoid contact with the eyes. In case of accidental contact, rinse eyes with large amounts of cool tap water.
- Some people have experienced changes in hair color and/or texture.
- It takes time to regrow hair. You may need to use this product 2 times a day for at least 4 months before you see results.
- The amount of hair regrowth is different for each person. This product will not work for everyone.

Stop use and ask a doctor if:

- Chest pain, rapid heartbeat, faintness, or dizziness occurs.
- Sudden, unexplained weight gain occurs.
- Your hands or feet swell.
- Scalp irritation or redness occurs.
- Unwanted facial hair growth occurs.
- You do not see hair regrowth in 4 months.

May be harmful if used when pregnant or breast-feeding. Keep out of reach of children. If swallowed, get medical help or contact a Poison Control Center right away.

What factors may increase the risk of serious side effects with Toppik Women's Hair Regrowth Treatment?

Toppik Women's Hair Regrowth Treatment should be applied only to the scalp. The risk of side effects may be greater when Toppik Women's Hair Regrowth Treatment is applied to other parts of the body.

Directions for Use:

When applying Toppik Women's Hair Regrowth Treatment make sure the medicine comes in direct contact with the scalp. The medicine will not work if it is sprayed only on your hair and does not reach your scalp. Carefully follow the instructions below to use the child-resistant sprayer pump to apply Toppik Women's Hair Regrowth Treatment.

1. Remove the bottle of Toppik Women's Hair Regrowth Treatment from the package.
2. Firmly hold the bottle upright with the turning wheel on the back of the bottle facing you. Push in the small tab located to the bottom right of the turning wheel.
3. While holding the tab in, press down on the top of the sprayer and turn the upper part of the sprayer with the turning wheel to the left until the spray nozzle is centered between the beveled grooves on the front of the bottle.
4. Then prime the sprayer by holding the bottle upright and pumping the sprayer 5 times to ensure delivery of a full spray. Be careful not to inhale the mist.
5. Aim the sprayer at your area of thinning hair or hair loss and pump the sprayer 6 times to apply a 1 mL dose twice a day.
6. After applying Toppik Women's Hair Regrowth Treatment, use the turning wheel to turn the sprayer cap back to the right to release the tab which places the sprayer nozzle behind the sprayer cap wall. Make sure the sprayer cannot be pushed or pumped before putting the bottle away.

If you have any other questions, ask your health care professional or call us at 1-800-THICKEN (844-2536). You can also email us at support@toppik.com or visit our website at TOPPIK.com.

Store at USP Controlled Room Temperature 20° to 25° C (68° to 77° F).

Save this leaflet for future reference.

PRINCIPAL DISPLAY PANEL - 60 mL Bottle Canister Label

NDC# 61355-569-60

WOMEN'S

Clinically proven to help regrow
hair. Reactivates hair follicles
to stimulate regrowth.

Toppik

Hair Regrowth Treatment
2% MINOXIDIL TOPICAL SOLUTION

Easy-To-Use
Spray
Unscented

TOPPIK INC.

60mL (2 fl oz) Bottle/ 30-Day Supply